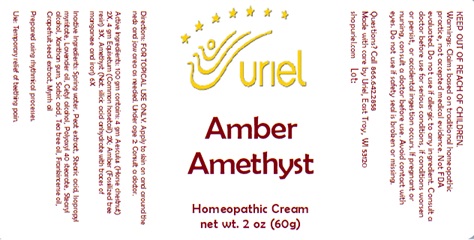 DRUG LABEL: Amber Amethyst
NDC: 48951-1270 | Form: CREAM
Manufacturer: Uriel Pharmacy Inc.
Category: homeopathic | Type: HUMAN OTC DRUG LABEL
Date: 20241204

ACTIVE INGREDIENTS: HORSE CHESTNUT 2 [hp_X]/1 g; EQUISETUM ARVENSE TOP 2 [hp_X]/1 g; AMBER 3 [hp_X]/1 g; SILICON DIOXIDE 6 [hp_X]/1 g
INACTIVE INGREDIENTS: SPHAGNUM SQUARROSUM PEAT; WATER; STEARIC ACID; ISOPROPYL MYRISTATE; LAVENDER OIL; CETYL ALCOHOL; POLYOXYL 40 STEARATE; STEARYL ALCOHOL; XANTHAN GUM; SORBIC ACID; FRANKINCENSE OIL; MYRRH OIL; CITRUS PARADISI SEED; TEA TREE OIL

Amber Amethyst

INDICATIONS AND USAGE

Directions: FOR TOPICAL USE ONLY.

DOSAGE AND ADMINISTRATION

Apply to skin on and around the neck and jaw area as needed. Under age 2: Consult a doctor.

ACTIVE INGREDIENT

Active Ingredients: 100 gm contains: 4 gm Aesculus (Horse chestnut) 2X, 4 gm Equisetum (Common horsetail) 2X; Amber (Fossilized tree resin) 3X, Amethyst (Nat. silicic acid anhydrate with traces of manganese and iron) 6X

INACTIVE INGREDIENT

Inactive Ingredients: Spring water, Peat extract, Stearic acid, Isopropyl myristate, Lavender oil, Cetyl alcohol, Polyoxyl 40 stearate, Stearyl alcohol, Xanthan gum, Sorbic acid, Tea tree oil, Frankincense oil, Grapefruit seed extract, Myrrh oil

Prepared using rhythmical processes.

PURPOSE

Use: Temporary relief of teething pain.

Warnings: FOR EXTERNAL USE ONLY.
Claims based on traditional homeopathic practice, not accepted medical evidence. Not FDA evaluated. Do not use if allergic to any ingredient. Consult a doctor before use for serious conditions, if conditions worsen or persist, or accidental ingestion occurs. If pregnant or nursing, consult a doctor before use. Avoid contact with eyes. Do not use if safety seal is broken or missing.

KEEP OUT OF REACH OF CHILDREN.

Questions? Call 866.642.2858
Made with care by Uriel, East Troy, WI 53120
shopuriel.com Lot: